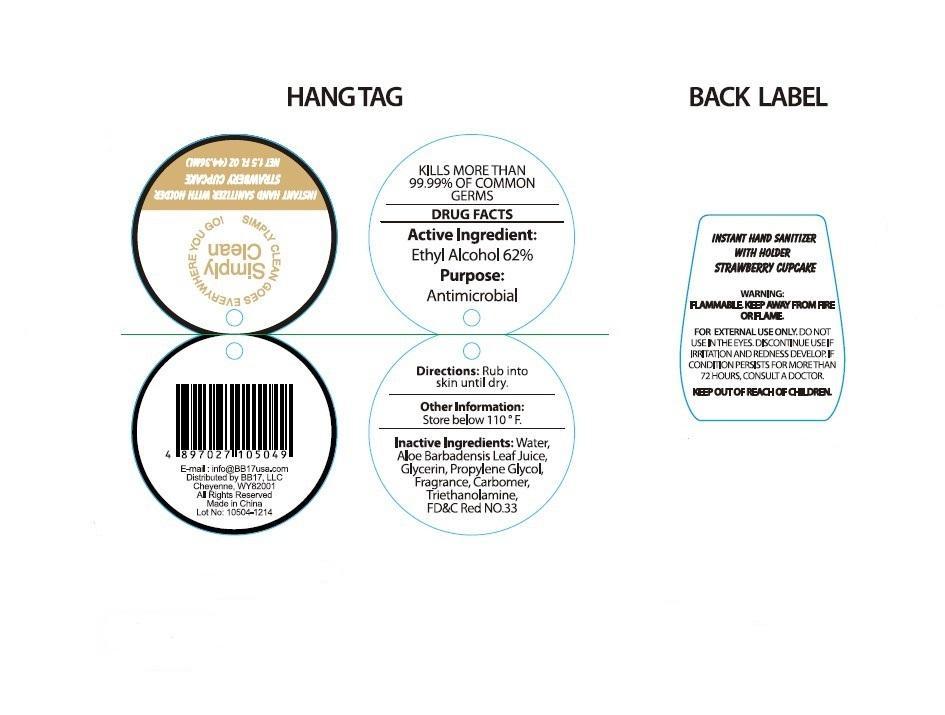 DRUG LABEL: Simply Clean Instant Hand Sanitizer  
                
NDC: 53603-1012 | Form: GEL
Manufacturer: BB17, LLC
Category: otc | Type: HUMAN OTC DRUG LABEL
Date: 20141226

ACTIVE INGREDIENTS: Alcohol 62 mL/100 mL
INACTIVE INGREDIENTS: WATER; GLYCERIN; PROPYLENE GLYCOL; CARBOMER INTERPOLYMER TYPE A (ALLYL SUCROSE CROSSLINKED); TROLAMINE; ALOE VERA LEAF; D&C RED NO. 33

Active Ingredients

Ethyl Alcohol 62%

Purpose
Antimicrobial

INDICATIONS AND USAGE

KILLS MORE THAN 99.99% OF COMMON GERMS

WARNING:
FLAMMABLE. KEEP AWAY FROM FIRE OR FLAME. FOR EXTERNAL USE ONLY.DO NOT USE IN THE EYES.

DISCONTINUE USE IF IRRITATION AND REDNESS DEVELOP.

IF CONDITION PERSISTS FOR MORE THAN 72 HOURS, CONSULT A DOCTOR.

KEEP OUT OF REACH OF CHILDREN.

DIRECTIONS:

Rub into skin until dry.

Other Information:

Store below 110 F.

Inactive Ingredients:

Water, Aloe barbadenis Leaf Juice, Glycerin,Propylene Glycol, Fragrance, Carbomer, Triethanolamine, FD&C Red No.33